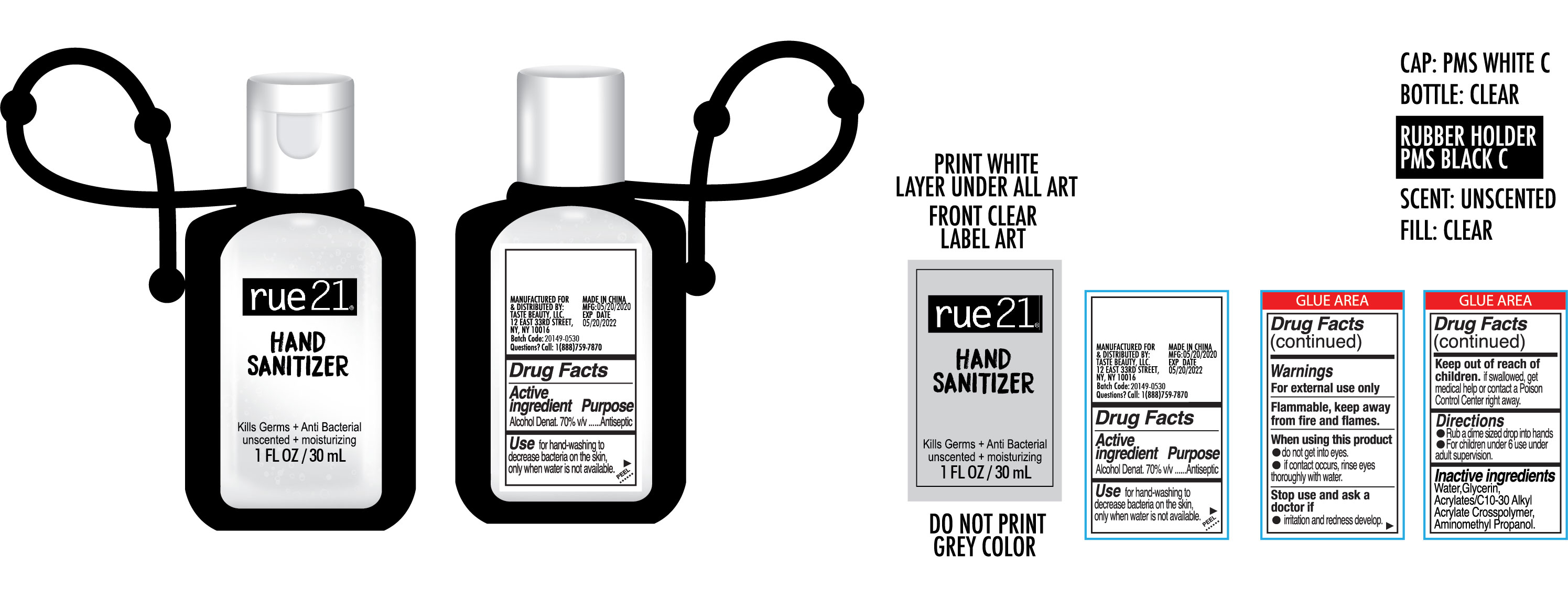 DRUG LABEL: Rue 21 Hand Sanitizer
NDC: 51522-007 | Form: GEL
Manufacturer: Gold Orient International Limited
Category: otc | Type: HUMAN OTC DRUG LABEL
Date: 20200529

ACTIVE INGREDIENTS: ALCOHOL 70 mL/100 mL
INACTIVE INGREDIENTS: GLYCERIN; WATER; CARBOMER COPOLYMER TYPE A (ALLYL PENTAERYTHRITOL CROSSLINKED); AMINOMETHYLPROPANOL

Active Ingredient(s)

Alcohol Denat 70% v/v. Purpose: Antiseptic

Purpose

Antiseptic, Hand Sanitizer

Use

For hand-washing to decrease bacteria on the skin only when water is not available

Warnings

For external use only. Flammable. Keep away from heat or flame

Do not use

- in children less than 2 months of age
- on open skin wounds

When using this product do not get into eyes. If contact occurs, rinse eyes thoroughly with water.

Stop use and ask a doctor if irritation or rash occurs.

Keep out of reach of children. If swallowed, get medical help or contact a Poison Control Center right away.

Directions

- Place enough product on hands to cover all surfaces. Rub hands together until dry.
- Supervise children under 6 years of age when using this product to avoid swallowing.

Inactive ingredients

Water, Glycerin, Acrylates/C10-30 Alkyl Acrylate Crosspolymer, Aminomethyl Propanol